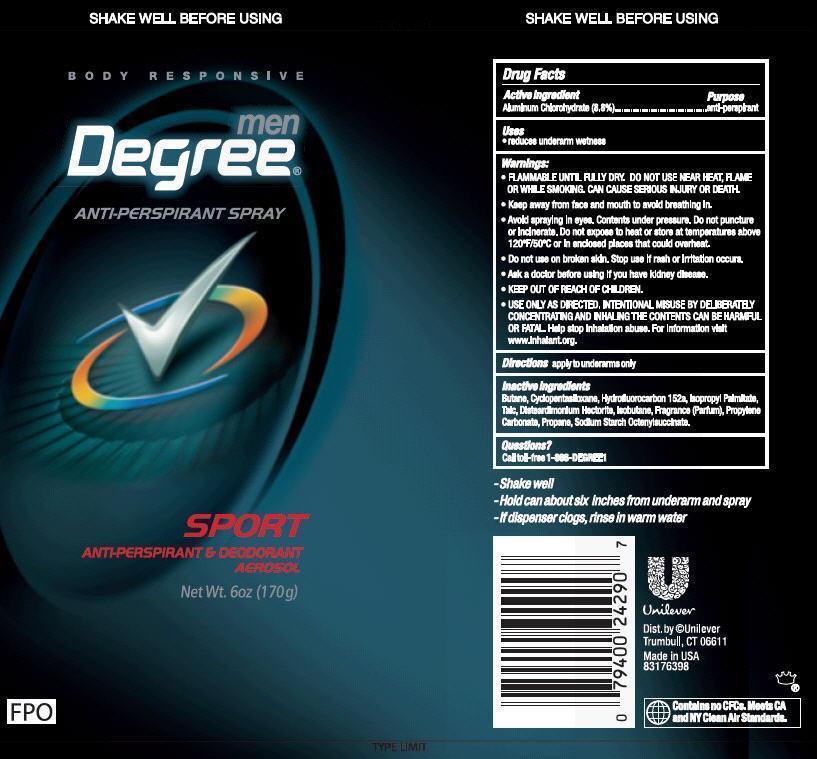 DRUG LABEL: Degree
NDC: 64942-1295 | Form: AEROSOL, SPRAY
Manufacturer: Conopco Inc. d/b/a Unilever
Category: otc | Type: HUMAN OTC DRUG LABEL
Date: 20130410

ACTIVE INGREDIENTS: Aluminum Chlorohydrate 8.8 g/100 g
INACTIVE INGREDIENTS: BUTANE; CYCLOMETHICONE 5; 1,1-DIFLUOROETHANE; ISOPROPYL PALMITATE; TALC; ISOBUTANE; PROPYLENE CARBONATE; PROPANE; DISTEARYLDIMONIUM CHLORIDE; HECTORITE

Degree Sport Aerosol Antiperspirant Deodorant

Active ingredient

Aluminum chlorohydrate (8.8%)

Purpose

anti-perspirant

Uses
reduces underarm wetness

WARNINGS:

- FLAMMABLE UNTIL FULLY DRY. DO NOT USE NEAR HEAT, FLAME OR WHILE SMOKING. CAN CAUSE SERIOUS INJURY OR DEATH.
- Keep away from face and mouth to avoid breathing in.
- Avoid spraying in eyes. Contents under pressure. Do not puncture or incinerate.Do not expose to heat or store at temperatures above 120°F/50°C or in enclosed places that could overheat.
- USE ONLY AS DIRECTED. INTENTIONAL MISUSE BY DELIBERATELY CONCENTRATING AND INHALING THE CONTENTS CAN BE HARMFUL OR FATAL. Help stop inhalation abuse. For information visit www.inhalant.org.

- Do not use on broken skin. Stop use if rash or irritation occurs.

- Ask a doctor before using if you have kidney disease.

- KEEP OUT OF REACH OF CHILDREN.

Directions

apply to underarms only

Inactive ingredients

Butane, Cyclopentasiloxane, Hydrofluorocarbon 152a, Isopropyl Palmitate, Talc, Disteardimonium Hectorite, Isobutane, Fragrance (Parfum), Propylene Carbonate, Propane, Sodium Starch Octenylsuccinate

Questions?
call toll-free 1-866-DEGREE1